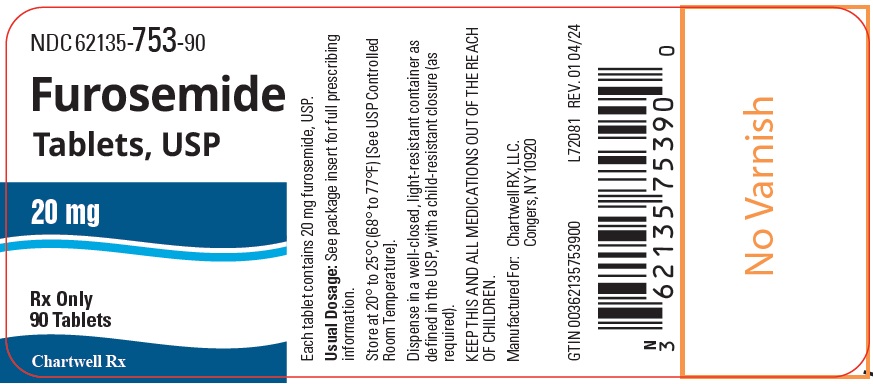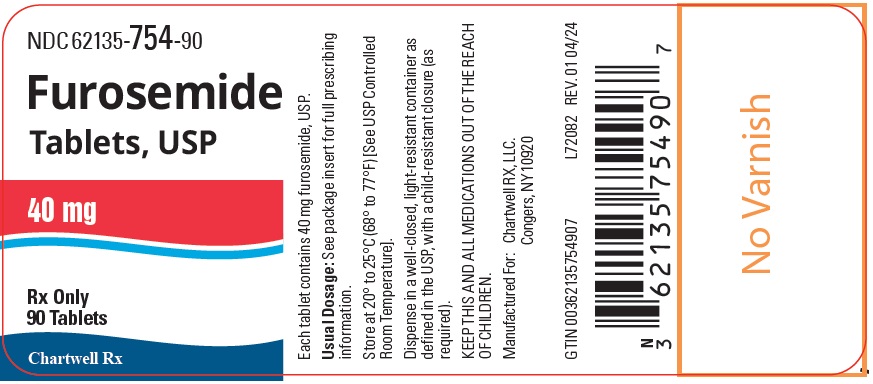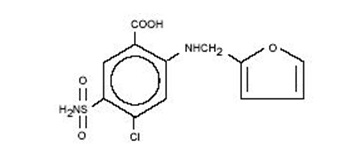 DRUG LABEL: Furosemide
NDC: 62135-753 | Form: TABLET
Manufacturer: Chartwell RX, LLC
Category: prescription | Type: HUMAN PRESCRIPTION DRUG LABEL
Date: 20250326

ACTIVE INGREDIENTS: FUROSEMIDE 20 mg/1 1
INACTIVE INGREDIENTS: SILICON DIOXIDE; STARCH, CORN; LACTOSE MONOHYDRATE; MAGNESIUM STEARATE; POVIDONE, UNSPECIFIED; SODIUM STARCH GLYCOLATE TYPE A

FUROSEMIDE TABLETS, USP

WARNING

Furosemide, USP is a potent diuretic which, if given in excessive amounts, can lead to a profound diuresis with water and electrolyte depletion. Therefore, careful medical supervision is required and dose and dose schedule must be adjusted to the individual patient’s needs (see DOSAGE AND ADMINISTRATION).

DESCRIPTION

Furosemide, USP is a diuretic which is an anthranilic acid derivative. Chemically, it is 4-chloro-N-furfuryl-5-sulfamoylanthranilic acid. Furosemide, USP is a white to slightly yellow, odorless, crystalline powder. It is practically insoluble in water, sparingly soluble in alcohol, freely soluble in solutions of dilute alkali hydroxides and insoluble in dilute acids.

The CAS Registry Number is 54-31-9.

The structural formula is as follows:

C12H11ClN2O5S M.W. 330.74

Each tablet, for oral administration, contains 20 mg or 40 mg Furosemide, USP. In addition, each tablet contains the following inactive ingredients: colloidal silicon dioxide, corn starch, lactose monohydrate, magnesium stearate, povidone, and sodium starch glycolate.

Both strengths: 20 mg and 40 mg meet USP Dissolution Test 1.

CLINICAL PHARMACOLOGY

Investigations into the mode of action of furosemide have utilized micropuncture studies in rats, stop flow experiments in dogs, and various clearance studies in both humans and experimental animals. It has been demonstrated that furosemide inhibits primarily the absorption of sodium and chloride not only in the proximal and distal tubules but also in the loop of Henle. The high degree of efficacy is largely due to the unique site of action. The action on the distal tubule is independent of any inhibitory effect on carbonic anhydrase and aldosterone.

Recent evidence suggests that furosemide glucuronide is the only or at least the major biotransformation product of furosemide in man. Furosemide is extensively bound to plasma proteins, mainly to albumin. Plasma concentrations ranging from 1 to 400 mcg/mL are 91 to 99% bound in healthy individuals. The unbound fraction averages 2.3 to 4.1% at therapeutic concentrations.

The onset of diuresis following oral administration is within 1 hour. The peak effect occurs within the first or second hour. The duration of diuretic effect is 6 to 8 hours.

In fasted normal men, the mean bioavailability of furosemide from furosemide tablets and furosemide oral solution is 64% and 60%, respectively, of that from an intravenous injection of the drug. Although furosemide is more rapidly absorbed from the oral solution (50 minutes) than from the tablet (87 minutes), peak plasma levels and area under the plasma concentration-time curves do not differ significantly. Peak plasma concentrations increase with increasing dose but times-to-peak do not differ among doses. The terminal half-life of furosemide is approximately 2 hours.

Significantly more furosemide is excreted in urine following the IV injection than after the tablet or oral solution. There are no significant differences between the two oral formulations in the amount of unchanged drug excreted in urine.

Geriatric Population

Furosemide binding to albumin may be reduced in elderly patients. Furosemide is predominantly excreted unchanged in the urine. The renal clearance of furosemide after intravenous administration in older healthy male subjects (60 to 70 years of age) is statistically significantly smaller than in younger healthy male subjects (20 to 35 years of age). The initial diuretic effect of furosemide in older subjects is decreased relative to younger subjects (see PRECAUTIONS, Geriatric Use).

INDICATIONS AND USAGE

Edema

Furosemide tablets are indicated in adults and pediatric patients for the treatment of edema associated with congestive heart failure, cirrhosis of the liver, and renal disease, including the nephrotic syndrome. Furosemide is particularly useful when an agent with greater diuretic potential is desired.

Hypertension

Oral furosemide may be used in adults for the treatment of hypertension alone or in combination with other antihypertensive agents. Hypertensive patients who cannot be adequately controlled with thiazides will probably also not be adequately controlled with furosemide alone.

CONTRAINDICATIONS

Furosemide is contraindicated in patients with anuria and in patients with a history of hypersensitivity to furosemide.

WARNINGS

In patients with hepatic cirrhosis and ascites, furosemide therapy is best initiated in the hospital. In hepatic coma and in states of electrolyte depletion, therapy should not be instituted until the basic condition is improved. Sudden alterations of fluid and electrolyte balance in patients with cirrhosis may precipitate hepatic coma; therefore, strict observation is necessary during the period of diuresis. Supplemental potassium chloride and, if required, an aldosterone antagonist are helpful in preventing hypokalemia and metabolic alkalosis.

If increasing azotemia and oliguria occur during treatment of severe progressive renal disease, furosemide should be discontinued.

Cases of tinnitus and reversible or irreversible hearing impairment and deafness have been reported. Reports usually indicate that furosemide ototoxicity is associated with rapid injection, severe renal impairment, the use of higher than recommended doses, hypoproteinemia or concomitant therapy with aminoglycoside antibiotics, ethacrynic acid, or other ototoxic drugs. If the physician elects to use high dose parenteral therapy, controlled intravenous infusion is advisable (for adults, an infusion rate not exceeding 4 mg furosemide per minute has been used) (see PRECAUTIONS, Drug Interactions).

PRECAUTIONS

General

Excessive diuresis may cause dehydration and blood volume reduction with circulatory collapse and possibly vascular thrombosis and embolism, particularly in elderly patients. As with any effective diuretic, electrolyte depletion may occur during furosemide therapy, especially in patients receiving higher doses and a restricted salt intake. Hypokalemia may develop with furosemide, especially with brisk diuresis, inadequate oral electrolyte intake, when cirrhosis is present, or during concomitant use of corticosteroids, ACTH, licorice in large amounts, or prolonged use of laxatives. Digitalis therapy may exaggerate metabolic effects of hypokalemia, especially myocardial effects.

All patients receiving furosemide therapy should be observed for these signs or symptoms of fluid or electrolyte imbalance (hyponatremia, hypochloremic alkalosis, hypokalemia, hypomagnesemia or hypocalcemia): dryness of mouth, thirst, weakness, lethargy, drowsiness, restlessness, muscle pains or cramps, muscular fatigue, hypotension, oliguria, tachycardia, arrhythmia, or gastrointestinal disturbances such as nausea and vomiting. Increases in blood glucose and alterations in glucose tolerance tests (with abnormalities of the fasting and 2 hour postprandial sugar) have been observed, and rarely, precipitation of diabetes mellitus has been reported.

In patients with severe symptoms of urinary retention (because of bladder emptying disorders, prostatic hyperplasia, urethral narrowing), the administration of furosemide can cause acute urinary retention related to increased production and retention of urine. Thus, these patients require careful monitoring, especially during the initial stages of treatment.

In patients at high risk for radiocontrast nephropathy furosemide can lead to a higher incidence of deterioration in renal function after receiving radiocontrast compared to high-risk patients who received only intravenous hydration prior to receiving radiocontrast.

In patients with hypoproteinemia (e.g., associated with nephrotic syndrome) the effect of furosemide may be weakened and its ototoxicity potentiated.

Asymptomatic hyperuricemia can occur and gout may rarely be precipitated.

Patients allergic to sulfonamides may also be allergic to furosemide. The possibility exists of exacerbation or activation of systemic lupus erythematosus.

As with many other drugs, patients should be observed regularly for the possible occurrence of blood dyscrasias, liver or kidney damage, or other idiosyncratic reactions.

Information for Patients

Patients receiving furosemide should be advised that they may experience symptoms from excessive fluid and/or electrolyte losses. The postural hypotension that sometimes occurs can usually be managed by getting up slowly. Potassium supplements and/or dietary measures may be needed to control or avoid hypokalemia.

Patients with diabetes mellitus should be told that furosemide may increase blood glucose levels and thereby affect urine glucose tests. The skin of some patients may be more sensitive to the effects of sunlight while taking furosemide.

Hypertensive patients should avoid medications that may increase blood pressure, including over-the-counter products for appetite suppression and cold symptoms.

Laboratory Tests

Serum electrolytes (particularly potassium), CO2, creatinine and BUN should be determined frequently during the first few months of furosemide therapy and periodically thereafter. Serum and urine electrolyte determinations are particularly important when the patient is vomiting profusely or receiving parenteral fluids. Abnormalities should be corrected or the drug temporarily withdrawn. Other medications may also influence serum electrolytes.

Reversible elevations of BUN may occur and are associated with dehydration, which should be avoided, particularly in patients with renal insufficiency.

Urine and blood glucose should be checked periodically in diabetics receiving furosemide, even in those suspected of latent diabetes.

Furosemide may lower serum levels of calcium (rarely cases of tetany have been reported) and magnesium. Accordingly, serum levels of these electrolytes should be determined periodically.

In premature infants furosemide may precipitate nephrocalcinosis/nephrolithiasis, therefore renal function must be monitored and renal ultrasonography performed (see PRECAUTIONS, Pediatric Use).

Drug Interactions

Furosemide may increase the ototoxic potential of aminoglycoside antibiotics, especially in the presence of impaired renal function. Except in life-threatening situations, avoid this combination.

Furosemide should not be used concomitantly with ethacrynic acid because of the possibility of ototoxicity. Patients receiving high doses of salicylates concomitantly with furosemide, as in rheumatic disease, may experience salicylate toxicity at lower doses because of competitive renal excretory sites.

There is a risk of ototoxic effects if cisplatin and furosemide are given concomitantly. In addition, nephrotoxicity of nephrotoxic drugs such as cisplatin may be enhanced if furosemide is not given in lower doses and with positive fluid balance when used to achieve forced diuresis during cisplatin treatment.

Furosemide has a tendency to antagonize the skeletal muscle relaxing effect of tubocurarine and may potentiate the action of succinylcholine.

Lithium generally should not be given with diuretics because they reduce lithium’s renal clearance and add a high risk of lithium toxicity.

Furosemide combined with angiotensin converting enzyme inhibitors or angiotensin II receptor blockers may lead to severe hypotension and deterioration in renal function, including renal failure. An interruption or reduction in the dosage of furosemide, angiotensin converting enzyme inhibitors, or angiotensin receptor blockers may be necessary.

Potentiation occurs with ganglionic or peripheral adrenergic blocking drugs.

Furosemide may decrease arterial responsiveness to norepinephrine. However, norepinephrine may still be used effectively.

Simultaneous administration of sucralfate and furosemide tablets may reduce the natriuretic and antihypertensive effects of furosemide. Patients receiving both drugs should be observed closely to determine if the desired diuretic and/or antihypertensive effect of furosemide is achieved. The intake of furosemide and sucralfate should be separated by at least two hours.

In isolated cases, intravenous administration of furosemide within 24 hours of taking chloral hydrate may lead to flushing, sweating attacks, restlessness, nausea, increase in blood pressure, and tachycardia. Use of furosemide concomitantly with chloral hydrate is therefore not recommended.

Phenytoin interferes directly with renal action of furosemide. There is evidence that treatment with phenytoin leads to decrease intestinal absorption of furosemide, and consequently to lower peak serum furosemide concentrations.

Methotrexate and other drugs that, like furosemide, undergo significant renal tubular secretion may reduce the effect of furosemide. Conversely, furosemide may decrease renal elimination of other drugs that undergo tubular secretion. High-dose treatment of both furosemide and these other drugs may result in elevated serum levels of these drugs and may potentiate their toxicity as well as the toxicity of furosemide.

Furosemide can increase the risk of cephalosporin-induced nephrotoxicity even in the setting of minor or transient renal impairment.

Concomitant use of cyclosporine and furosemide is associated with increased risk of gouty arthritis secondary to furosemide-induced hyperurecemia and cyclosporine impairment of renal urate excretion.

One study in six subjects demonstrated that the combination of furosemide and acetylsalicylic acid temporarily reduced creatinine clearance in patients with chronic renal insufficiency. There are case reports of patients who developed increased BUN, serum creatinine and serum potassium levels, and weight gain when furosemide was used in conjunction with NSAIDs.

Literature reports indicate that coadministration of indomethacin may reduce the natriuretic and antihypertensive effects of furosemide in some patients by inhibiting prostaglandin synthesis. Indomethacin may also affect plasma renin levels, aldosterone excretion, and renin profile evaluation. Patients receiving both indomethacin and furosemide should be observed closely to determine if the desired diuretic and/or antihypertensive effect of furosemide is achieved.

Carcinogenesis, Mutagenesis, Impairment of Fertility

Furosemide was tested for carcinogenicity by oral administration in one strain of mice and one strain of rats. A small but significantly increased incidence of mammary gland carcinomas occurred in female mice at a dose 17.5 times the maximum human dose of 600 mg. There were marginal increases in uncommon tumors in male rats at a dose of 15 mg/kg (slightly greater than the maximum human dose) but not at 30 mg/kg.

Furosemide was devoid of mutagenic activity in various strains of Salmonella typhimuriumwhen tested in the presence or absence of an in vitrometabolic activation system, and questionably positive for gene mutation in mouse lymphoma cells in the presence of rat liver S9 at the highest dose tested. Furosemide did not induce sister chromatid exchange in human cells in vitro, but other studies on chromosomal aberrations in human cells in vitrogave conflicting results. In Chinese hamster cells it induced chromosomal damage but was questionably positive for sister chromatid exchange. Studies on the induction by furosemide of chromosomal aberrations in mice were inconclusive. The urine of rats treated with this drug did not induce gene conversion in Saccharomyces cerevisiae.

Furosemide produced no impairment of fertility in male or female rats, at 100 mg/kg/day (the maximum effective diuretic dose in the rat and 8 times the maximal human dose of 600 mg/day).

Pregnancy

Teratogenic Effects

Pregnancy Category C

Furosemide has been shown to cause unexplained maternal deaths and abortions in rabbits at 2, 4, and 8 times the maximal recommended human dose. There are no adequate and well-controlled studies in pregnant women. Furosemide should be used during pregnancy only if the potential benefit justifies the potential risk to the fetus.

Treatment during pregnancy requires monitoring of fetal growth because of the potential for higher birth weights.

The effects of furosemide on embryonic and fetal development and on pregnant dams were studied in mice, rats, and rabbits.

Furosemide caused unexplained maternal deaths and abortions in the rabbit at the lowest dose of 25 mg/kg (two times the maximal recommended human dose of 600 mg/day). In another study, a dose of 50 mg/kg (four times the maximal recommended human dose of 600 mg/day) also caused maternal deaths and abortions when administered to rabbits between Days 12 and 17 of gestation. In a third study, none of the pregnant rabbits survived a dose of 100 mg/kg. Data from the above studies indicate fetal lethality that can precede maternal deaths.

The results of the mouse study and one of the three rabbit studies also showed an increased incidence and severity of hydronephrosis (distention of the renal pelvis and, in some cases, of the ureters) in fetuses derived from the treated dams as compared with the incidence in fetuses from the control group.

Nursing Mothers

Because it appears in breast milk, caution should be exercised when furosemide is administered to a nursing mother.

Furosemide may inhibit lactation.

Pediatric Use

In premature infants furosemide may precipitate nephrocalcinosis/nephrolithiasis. Nephrocalcinosis/nephrolithiasis has also been observed in children under 4 years of age with no history of prematurity who have been treated chronically with furosemide. Monitor renal function, and renal ultrasonography should be considered, in pediatric patients receiving furosemide.

If furosemide is administered to premature infants during the first weeks of life, it may increase the risk of persistence of patent ductus arteriosus.

Geriatric Use

Controlled clinical studies of furosemide did not include sufficient numbers of subjects aged 65 and over to determine whether they respond differently from younger subjects. Other reported clinical experience has not identified differences in response between the elderly and younger patients. In general, dose selection for the elderly patient should be cautious, usually starting at the low end of the dosing range, reflecting the greater frequency of decreased hepatic, renal or cardiac function, and of concomitant disease or other drug therapy.

This drug is known to be substantially excreted by the kidney, and the risk of toxic reactions to this drug may be greater in patients with impaired renal function. Because elderly patients are more likely to have decreased renal function, care should be taken in dose selection and it may be useful to monitor renal function (see PRECAUTIONS, Generaland DOSAGE AND ADMINISTRATION).

ADVERSE REACTIONS

Adverse reactions are categorized below by organ system and listed by decreasing severity.

Gastrointestinal System Reactions

1. hepatic encephalopathy in patients with hepato-cellular insufficiency
2. pancreatitis
3. jaundice (intrahepatic cholestatic jaundice)
4. increased liver enzymes
5. anorexia
6. oral and gastric irritation
7. cramping
8. diarrhea
9. constipation
10. nausea
11. vomiting

Systemic Hypersensitivity Reactions

1. Severe anaphylactic or anaphylactoid reactions (e.g. with shock)
2. systemic vasculitis
3. interstitial nephritis
4. necrotizing angiitis

Central Nervous System Reactions

1. tinnitus and hearing loss
2. paresthesias
3. vertigo
4. dizziness
5. headache
6. blurred vision
7. xanthopsia

Hematologic Reactions

1. aplastic anemia
2. thrombocytopenia
3. agranulocytosis
4. hemolytic anemia
5. leukopenia
6. anemia
7. eosinophilia

Dermatologic-Hypersensitivity Reactions

1. toxic epidermal necrolysis
2. Stevens-Johnson Syndrome
3. erythema multiforme
4. drug rash with eosinophilia and systemic symptoms
5. acute generalized exanthematous pustulosis
6. exfoliative dermatitis
7. bullous pemphigoid
8. purpura
9. photosensitivity
10. rash
11. pruritis
12. urticaria

Cardiovascular Reaction

1. Orthostatic hypotension may occur and be aggravated by alcohol, barbiturates or narcotics.
2. Increase in cholesterol and triglyceride serum levels

Other Reactions

1. hyperglycemia
2. glycosuria
3. hyperuricemia
4. muscle spasm
5. weakness
6. restlessness
7. urinary bladder spasm
8. thrombophlebitis
9. fever

Whenever adverse reactions are moderate or severe, furosemide dosage should be reduced or therapy withdrawn.

OVERDOSAGE

The principal signs and symptoms of overdosage with furosemide are dehydration, blood volume reduction, hypotension, electrolyte imbalance, hypokalemia and hypochloremic alkalosis, and are extensions of its diuretic action.

The acute toxicity of furosemide has been determined in mice, rats and dogs. In all three, the oral LD50exceeded 1000 mg/kg body weight, while the intravenous LD50ranged from 300 to 680 mg/kg. The acute intragastric toxicity in neonatal rats is 7 to 10 times that of adult rats.

The concentration of furosemide in biological fluid associated with toxicity or death is not known.

Treatment of overdosage is supportive and consists of replacement of excessive fluids and electrolyte losses. Serum electrolytes, carbon dioxide level and blood pressure should be determined frequently. Adequate drainage must be assured in patients with urinary bladder outlet obstruction (such as prostatic hypertrophy).

Hemodialysis does not accelerate furosemide elimination.

DOSAGE AND ADMINISTRATION

Edema

Therapy should be individualized according to patient response to gain maximal therapeutic response and to determine the minimal dose needed to maintain that response.

Adults

The usual initial dose of oral furosemide is 20 to 80 mg given as a single dose. Ordinarily a prompt diuresis ensues. If needed, the same dose can be administered 6 to 8 hours later or the dose may be increased. The dose may be raised by 20 or 40 mg and given not sooner than 6 to 8 hours after the previous dose until the desired diuretic effect has been obtained. The individually determined single dose should then be given once or twice daily (e.g., at 8 a.m. and 2 p.m.). The dose of furosemide may be carefully titrated up to 600 mg/day in patients with clinically severe edematous states.

Edema may be most efficiently and safely mobilized by giving furosemide on 2 to 4 consecutive days each week.

When doses exceeding 80 mg/day are given for prolonged periods, careful clinical observation and laboratory monitoring are particularly advisable (see PRECAUTIONS, Laboratory Tests).

Geriatric Patients

In general, dose selection for the elderly patient should be cautious, usually starting at the low end of the dosing range (see PRECAUTIONS, Geriatric Use).

Pediatric Patients

The usual initial dose of oral furosemide in pediatric patients is 2 mg/kg body weight given as a single dose. If the diuretic response is not satisfactory after the initial dose, dosage may be increased by 1 or 2 mg/kg no sooner than 6 to 8 hours after the previous dose. Doses greater than 6 mg/kg body weight are not recommended. For maintenance therapy in pediatric patients, the dose should be adjusted to the minimum effective level.

Hypertension

Therapy should be individualized according to the patient’s response to gain maximal therapeutic response and to determine the minimal dose needed to maintain that therapeutic response.

Adults

The usual initial dose of furosemide for hypertension is 80 mg, usually divided into 40 mg twice a day. Dosage should then be adjusted according to response. If response is not satisfactory, add other antihypertensive agents.

Changes in blood pressure must be carefully monitored when furosemide is used with other antihypertensive drugs, especially during initial therapy. To prevent excessive drop in blood pressure, the dosage of other agents should be reduced by at least 50 percent when furosemide is added to the regimen. As the blood pressure falls under the potentiating effect of furosemide, a further reduction in dosage or even discontinuation of other antihypertensive drugs may be necessary.

Geriatric Patients

In general, dose selection and dose adjustment for the elderly patient should be cautious, usually starting at the low end of the dosing range (see PRECAUTIONS, Geriatric Use).

HOW SUPPLIED

Furosemide Tablets, USP 20 mg are available as white, round, flat face, beveled edge, tablets debossed “ CE” on one side and “ 174” on the other side, containing 20 mg of Furosemide, USP and supplied as follows:

NDC 62135-753-90 in bottles of 90 tablets

Furosemide Tablets, USP 40 mg are available as white, round, flat face, beveled edge bisected debossed with “ CE” on one side of the break line and " 175" on the other side containing 40 mg of Furosemide, USP and supplied as follows:

NDC 62135-754-90 in bottles of 90 tablets

Dispense in a well-closed, light-resistant container as defined in the USP, with a child-resistant closure (as required). Exposure to light may cause slight discoloration. Discolored tablets should not be dispensed.

Store at 20° to 25°C (68° to 77°F) [See USP Controlled Room Temperature].

KEEP THIS AND ALL MEDICATIONS OUT OF THE REACH OF CHILDREN.

Manufactured For:
Chartwell RX, LLC
Congers, NY 10920

Rev. 04/2024

L72083

PRINCIPAL DISPLAY PANEL

Furosemide Tablets, USP 20 mg - NDC 62135-753-90 - 90s Bottle Label

Furosemide Tablets, USP 40 mg - NDC 62135-754-90 - 90s Bottle Label